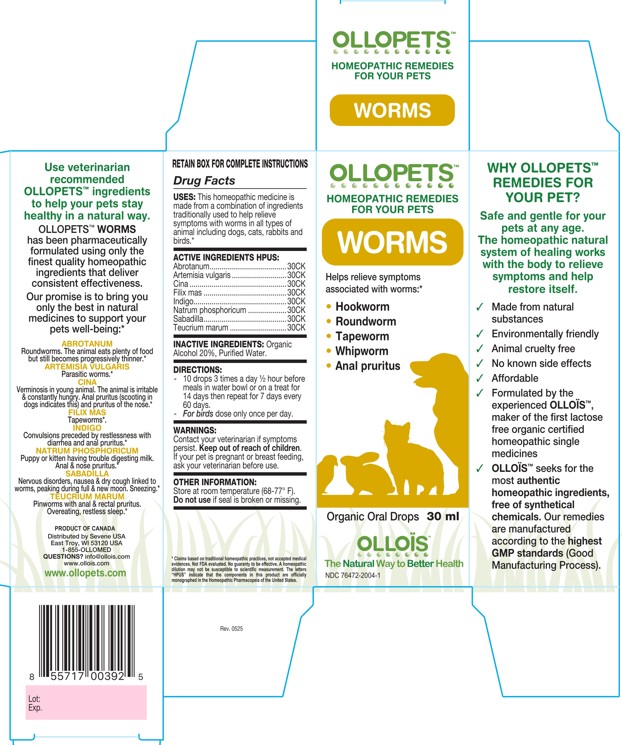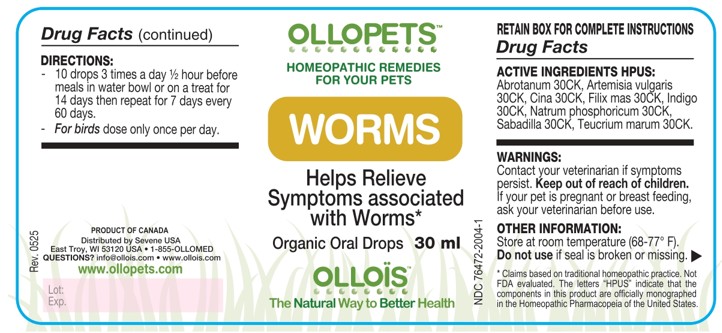 DRUG LABEL: OLLOPETS WORMS
NDC: 76472-2004 | Form: SOLUTION
Manufacturer: SEVENE USA
Category: homeopathic | Type: OTC ANIMAL DRUG LABEL
Date: 20260218

ACTIVE INGREDIENTS: ARTEMISIA ABROTANUM FLOWERING TOP 30 [hp_C]/100 mL; ARTEMISIA VULGARIS ROOT 30 [hp_C]/100 mL; ARTEMISIA CINA PRE-FLOWERING TOP 30 [hp_C]/100 mL; DRYOPTERIS FILIX-MAS ROOT 30 [hp_C]/100 mL; INDIGOFERA TINCTORIA WHOLE 30 [hp_C]/100 mL; SODIUM PHOSPHATE, DIBASIC, HEPTAHYDRATE 30 [hp_C]/100 mL; SCHOENOCAULON OFFICINALE SEED 30 [hp_C]/100 mL; TEUCRIUM MARUM 30 [hp_C]/100 mL
INACTIVE INGREDIENTS: ALCOHOL; WATER

SEVENE USA - OLLOPETS - WORMS

ACTIVE INGREDIENT HPUS

Abrotanum.........................................30K
Artemisia vulgaris ..............................30K
Cina ...................................................30K
Filix mas ............................................30K
Indigo.................................................30K
Natrum phosphoricum ......................30K
Sabadilla............................................30K
Teucrium marum ...............................30K